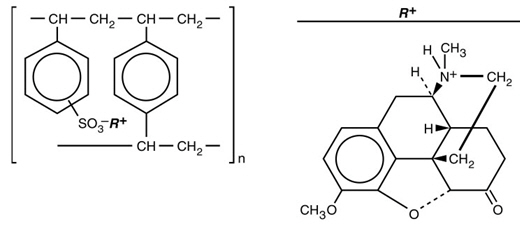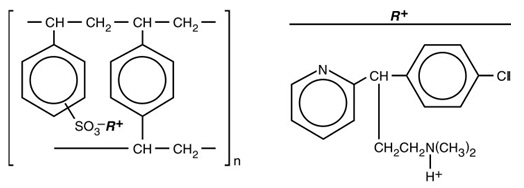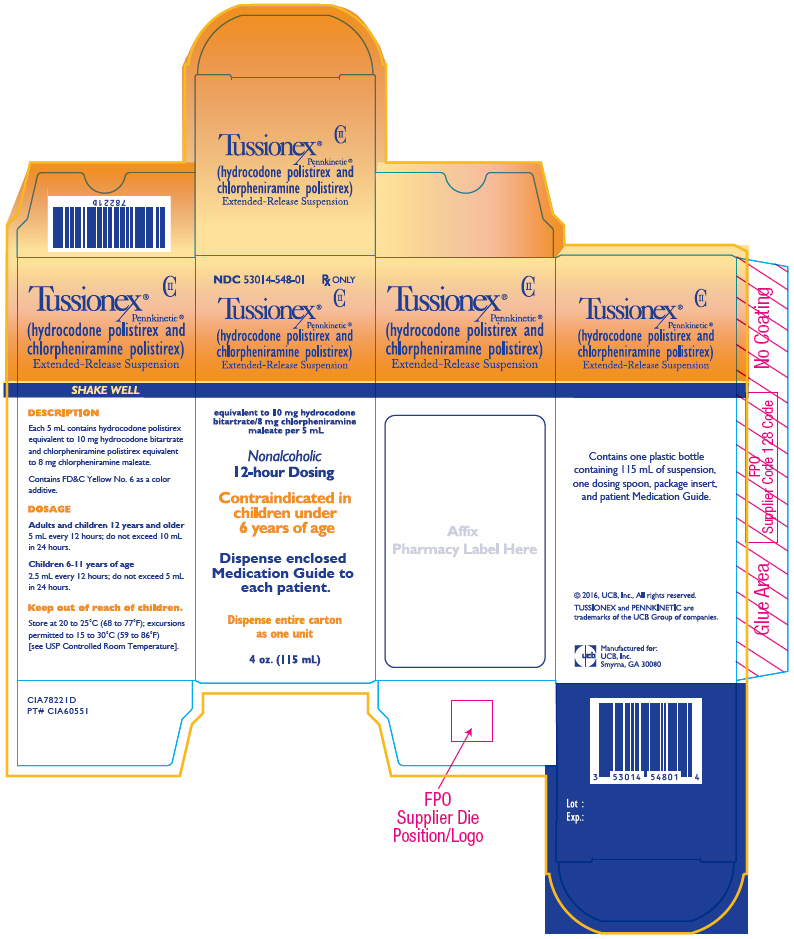 DRUG LABEL: Tussionex Pennkinetic
NDC: 53014-548 | Form: SUSPENSION, EXTENDED RELEASE
Manufacturer: Unither Manufacturing LLC
Category: prescription | Type: HUMAN PRESCRIPTION DRUG LABEL
Date: 20170120
DEA Schedule: CII

ACTIVE INGREDIENTS: hydrocodone 10 mg/5 mL; chlorpheniramine 8 mg/5 mL
INACTIVE INGREDIENTS: ascorbic acid; D&C Yellow No. 10; ethylcellulose, unspecified; FD&C Yellow No. 6; high fructose corn syrup; methylparaben; polyethylene glycol 3350; polysorbate 80; starch, corn; propylene glycol; propylparaben; water; sucrose; xanthan gum

Tussionex®
Pennkinetic®
(hydrocodone polistirex and chlorpheniramine polistirex)
Extended-Release Suspension CII

Rx only

BOXED WARNING

WARNING: RISKS FROM CONCOMITANT USE WITH BENZODIAZEPINES OR OTHER CNS DEPRESSANTS

Concomitant use of opioids with benzodiazepine or other central nervous system (CNS) depressants, including alcohol, may result in profound sedation, respiratory depression, coma, and death (see WARNINGS and PRECAUTIONS – Drug Interactions). Avoid use of opioid cough medications in patients taking benzodiazepines, other CNS depressants, or alcohol.

DESCRIPTION

Each 5 mL of TUSSIONEX Pennkinetic Extended-Release Suspension contains hydrocodone polistirex equivalent to 10 mg of hydrocodone bitartrate and chlorpheniramine polistirex equivalent to 8 mg of chlorpheniramine maleate. Hydrocodone is a centrally-acting narcotic antitussive. Chlorpheniramine is an antihistamine. TUSSIONEX Pennkinetic Extended-Release Suspension is for oral use only.

Hydrocodone Polistirex

Sulfonated styrene-divinylbenzene copolymer complex with 4,5α-epoxy-3-methoxy-17-methylmorphinan-6-one.

Chlorpheniramine Polistirex

Sulfonated styrene-divinylbenzene copolymer complex with 2-[p-chloro-α-[2-(dimethylamino)ethyl]-benzyl]pyridine.

Inactive Ingredients

Ascorbic acid, D&C Yellow No. 10, ethylcellulose, FD&C Yellow No. 6, flavor, high fructose corn syrup, methylparaben, polyethylene glycol 3350, polysorbate 80, pregelatinized starch, propylene glycol, propylparaben, purified water, sucrose, vegetable oil, xanthan gum.

CLINICAL PHARMACOLOGY

Hydrocodone is a semisynthetic narcotic antitussive and analgesic with multiple actions qualitatively similar to those of codeine. The precise mechanism of action of hydrocodone and other opiates is not known; however, hydrocodone is believed to act directly on the cough center. In excessive doses, hydrocodone, like other opium derivatives, will depress respiration. The effects of hydrocodone in therapeutic doses on the cardiovascular system are insignificant. Hydrocodone can produce miosis, euphoria, and physical and psychological dependence.

Chlorpheniramine is an antihistamine drug (H1 receptor antagonist) that also possesses anticholinergic and sedative activity. It prevents released histamine from dilating capillaries and causing edema of the respiratory mucosa.

Hydrocodone release from TUSSIONEX Pennkinetic Extended-Release Suspension is controlled by the Pennkinetic System, an extended-release drug delivery system, which combines an ion-exchange polymer matrix with a diffusion rate-limiting permeable coating. Chlorpheniramine release is prolonged by use of an ion-exchange polymer system.

Following multiple dosing with TUSSIONEX Pennkinetic Extended-Release Suspension, hydrocodone mean (S.D.) peak plasma concentrations of 22.8 (5.9) ng/mL occurred at 3.4 hours. Chlorpheniramine mean (S.D.) peak plasma concentrations of 58.4 (14.7) ng/mL occurred at 6.3 hours following multiple dosing. Peak plasma levels obtained with an immediate-release syrup occurred at approximately 1.5 hours for hydrocodone and 2.8 hours for chlorpheniramine. The plasma half-lives of hydrocodone and chlorpheniramine have been reported to be approximately 4 and 16 hours, respectively.

INDICATIONS AND USAGE

TUSSIONEX Pennkinetic Extended-Release Suspension is indicated for relief of cough and upper respiratory symptoms associated with allergy or a cold in adults and children 6 years of age and older.

CONTRAINDICATIONS

TUSSIONEX Pennkinetic Extended-Release Suspension is contraindicated in patients with a known allergy or sensitivity to hydrocodone or chlorpheniramine.

The use of TUSSIONEX Pennkinetic Extended-Release Suspension is contraindicated in children less than 6 years of age due to the risk of fatal respiratory depression.

WARNINGS

Risk from Concomitant Use with Benzodiazepines or other CNS Depressants

Concomitant use of opioids, including TUSSIONEX Pennkinetic Extended-Release Suspension, with benzodiazepines, or other CNS depressants, including alcohol, may result in profound sedation, respiratory depression, coma, and death. Because of these risks, avoid use of opioid cough medications in patients taking benzodiazepines, other CNS depressants, or alcohol (see PRECAUTIONS – Drug Interactions).

Observational studies have demonstrated that concomitant use of opioid analgesics and benzodiazepines increases the risk of drug-related mortality compared to use of opioids alone. Because of similar pharmacologic properties, it is reasonable to expect similar risk with concomitant use of opioid cough medications and benzodiazepines, other CNS depressants, or alcohol.

Advise both patients and caregivers about the risks of respiratory depression and sedation if TUSSIONEX Pennkinetic Extended-Release Suspension is used with benzodiazepines, alcohol, or other CNS depressants (see PRECAUTIONS – Information for Patients).

Respiratory Depression

As with all narcotics, TUSSIONEX Pennkinetic Extended-Release Suspension produces dose-related respiratory depression by directly acting on brain stem respiratory centers. Hydrocodone affects the center that controls respiratory rhythm and may produce irregular and periodic breathing. Caution should be exercised when TUSSIONEX Pennkinetic Extended-Release Suspension is used postoperatively and in patients with pulmonary disease, or whenever ventilatory function is depressed. If respiratory depression occurs, it may be antagonized by the use of naloxone hydrochloride and other supportive measures when indicated (see OVERDOSAGE).

Head Injury and Increased Intracranial Pressure

The respiratory depressant effects of narcotics and their capacity to elevate cerebrospinal fluid pressure may be markedly exaggerated in the presence of head injury, other intracranial lesions, or a pre-existing increase in intracranial pressure. Furthermore, narcotics produce adverse reactions, which may obscure the clinical course of patients with head injuries.

Acute Abdominal Conditions

The administration of narcotics may obscure the diagnosis or clinical course of patients with acute abdominal conditions.

Obstructive Bowel Disease

Chronic use of narcotics may result in obstructive bowel disease especially in patients with underlying intestinal motility disorder.

Pediatric Use

The use of TUSSIONEX Pennkinetic Extended-Release Suspension is contraindicated in children less than 6 years of age (see CONTRAINDICATIONS).

In pediatric patients, as well as adults, the respiratory center is sensitive to the depressant action of narcotic cough suppressants in a dose-dependent manner. Caution should be exercised when administering TUSSIONEX Pennkinetic Extended-Release Suspension to pediatric patients 6 years of age and older. Overdose or concomitant administration of TUSSIONEX Pennkinetic Extended-Release Suspension with other respiratory depressants may increase the risk of respiratory depression in pediatric patients. Benefit to risk ratio should be carefully considered, especially in pediatric patients with respiratory embarrassment (e.g., croup) (see PRECAUTIONS).

PRECAUTIONS

General

Caution is advised when prescribing this drug to patients with narrow-angle glaucoma, asthma, or prostatic hypertrophy.

Special Risk Patients

As with any narcotic agent, TUSSIONEX Pennkinetic Extended-Release Suspension should be used with caution in elderly or debilitated patients and those with severe impairment of hepatic or renal function, hypothyroidism, Addison's disease, prostatic hypertrophy, or urethral stricture. The usual precautions should be observed and the possibility of respiratory depression should be kept in mind.

Information for Patients

Advise the patient to read the FDA-approved patient labeling (Medication Guide).

Concomitant Use with Benzodiazepines or Other CNS Depressants

Inform patients and caregivers that potentially fatal additive effects may occur if TUSSIONEX Pennkinetic Extended-Release Suspension is used with benzodiazepines or other CNS depressants, including alcohol. Because of this risk, patients should avoid concomitant use of TUSSIONEX Pennkinetic Extended-Release Suspension with benzodiazepines or other CNS depressants, including alcohol (see WARNINGS and PRECAUTIONS – Drug Interactions).

Neurological Adverse Reactions

Advise patients that TUSSIONEX Pennkinetic Extended-Release Suspension may produce marked drowsiness and impair the mental and/or physical abilities required for the performance of potentially hazardous tasks such as driving a car or operating machinery. Advise patients to avoid driving or operating machinery during treatment with TUSSIONEX Pennkinetic Extended-Release Suspension.

Dosing Instructions

Advise patients not to dilute TUSSIONEX Pennkinetic Extended-Release Suspension with other fluids and not to mix with other drugs as this may alter the resin-binding and change the absorption rate, possibly increasing the toxicity.

Advise patients that TUSSIONEX Pennkinetic Extended-Release Suspension should be measured with an accurate measuring device. A household teaspoon is not an accurate measuring device and could lead to overdosage. A dosing spoon is provided with the 4 oz (115 mL) packaged product. One side of the spoon is for a 2.5 mL dose. The other side of the spoon is for a 5 mL dose. Instruct the patient to fill to level the side of the spoon for the dose that has been prescribed. The spoon should not be overfilled. Rinse the measuring device or dosing spoon after each use.

Alternatively, a pharmacist can recommend an appropriate measuring device and can provide instructions for measuring the correct dose.

Cough Reflex

Hydrocodone suppresses the cough reflex; as with all narcotics, caution should be exercised when TUSSIONEX Pennkinetic Extended-Release Suspension is used postoperatively, and in patients with pulmonary disease.

Drug Interactions

The use of benzodiazepines, opioids, antihistamines, antipsychotics, anti-anxiety agents, or other CNS depressants (including alcohol) concomitantly with TUSSIONEX Pennkinetic Extended-Release Suspension may cause an additive CNS depressant effect, profound sedation, respiratory depression, coma, and death and should be avoided (see WARNINGS).

The use of MAO inhibitors or tricyclic antidepressants with hydrocodone preparations may increase the effect of either the antidepressant or hydrocodone.

The concurrent use of other anticholinergics with hydrocodone may produce paralytic ileus.

Carcinogenesis, Mutagenesis, Impairment of Fertility

Carcinogenicity, mutagenicity, and reproductive studies have not been conducted with TUSSIONEX Pennkinetic Extended-Release Suspension.

Pregnancy

Teratogenic Effects

Pregnancy Category C

Hydrocodone has been shown to be teratogenic in hamsters when given in doses 700 times the human dose. There are no adequate and well-controlled studies in pregnant women. TUSSIONEX Pennkinetic Extended-Release Suspension should be used during pregnancy only if the potential benefit justifies the potential risk to the fetus.

Nonteratogenic Effects

Babies born to mothers who have been taking opioids regularly prior to delivery will be physically dependent. The withdrawal signs include irritability and excessive crying, tremors, hyperactive reflexes, increased respiratory rate, increased stools, sneezing, yawning, vomiting, and fever. The intensity of the syndrome does not always correlate with the duration of maternal opioid use or dose.

Labor and Delivery

As with all narcotics, administration of TUSSIONEX Pennkinetic Extended-Release Suspension to the mother shortly before delivery may result in some degree of respiratory depression in the newborn, especially if higher doses are used.

Nursing Mothers

It is not known whether this drug is excreted in human milk. Because many drugs are excreted in human milk and because of the potential for serious adverse reactions in nursing infants from TUSSIONEX Pennkinetic Extended-Release Suspension, a decision should be made whether to discontinue nursing or to discontinue the drug, taking into account the importance of the drug to the mother.

Pediatric Use

The use of TUSSIONEX Pennkinetic Extended-Release Suspension is contraindicated in children less than 6 years of age (see CONTRAINDICATIONS and ADVERSE REACTIONS, Respiratory, Thoracic and Mediastinal Disorders).

TUSSIONEX Pennkinetic Extended-Release Suspension should be used with caution in pediatric patients 6 years of age and older (see WARNINGS, Pediatric Use).

Geriatric Use

Clinical studies of TUSSIONEX did not include sufficient numbers of subjects aged 65 and over to determine whether they respond differently from younger subjects. Other reported clinical experience has not identified differences in responses between the elderly and younger patients. In general, dose selection for an elderly patient should be cautious, usually starting at the low end of the dosing range, reflecting the greater frequency of decreased hepatic, renal, or cardiac function, and of concomitant disease or other drug therapy.

This drug is known to be substantially excreted by the kidney, and the risk of toxic reactions to this drug may be greater in patients with impaired renal function. Because elderly patients are more likely to have decreased renal function, care should be taken in dose selection, and it may be useful to monitor renal function.

ADVERSE REACTIONS

Gastrointestinal Disorders

Nausea and vomiting may occur; they are more frequent in ambulatory than in recumbent patients. Prolonged administration of TUSSIONEX Pennkinetic Extended-Release Suspension may produce constipation.

General Disorders and Administration Site Conditions

Death

Nervous System Disorders

Sedation, drowsiness, mental clouding, lethargy, impairment of mental and physical performance, anxiety, fear, dysphoria, euphoria, dizziness, psychic dependence, mood changes.

Renal and Urinary Disorders

Ureteral spasm, spasm of vesical sphincters, and urinary retention have been reported with opiates.

Respiratory, Thoracic and Mediastinal Disorders

Dryness of the pharynx, occasional tightness of the chest, and respiratory depression (see CONTRAINDICATIONS).

TUSSIONEX Pennkinetic Extended-Release Suspension may produce dose-related respiratory depression by acting directly on brain stem respiratory centers (see OVERDOSAGE). Use of TUSSIONEX Pennkinetic Extended-Release Suspension in children less than 6 years of age has been associated with fatal respiratory depression. Overdose with TUSSIONEX Pennkinetic Extended-Release Suspension in children 6 years of age and older, in adolescents, and in adults has been associated with fatal respiratory depression.

Skin and Subcutaneous Tissue Disorders

Rash, pruritus.

DRUG ABUSE AND DEPENDENCE

TUSSIONEX Pennkinetic Extended-Release Suspension is a Schedule II narcotic. Psychic dependence, physical dependence and tolerance may develop upon repeated administration of narcotics; therefore, TUSSIONEX Pennkinetic Extended-Release Suspension should be prescribed and administered with caution. However, psychic dependence is unlikely to develop when TUSSIONEX Pennkinetic Extended-Release Suspension is used for a short time for the treatment of cough. Physical dependence, the condition in which continued administration of the drug is required to prevent the appearance of a withdrawal syndrome, assumes clinically significant proportions only after several weeks of continued oral narcotic use, although some mild degree of physical dependence may develop after a few days of narcotic therapy.

OVERDOSAGE

Signs and Symptoms

Serious overdosage with hydrocodone is characterized by respiratory depression (a decrease in respiratory rate and/or tidal volume, Cheyne-Stokes respiration, cyanosis), extreme somnolence progressing to stupor or coma, skeletal muscle flaccidity, cold and clammy skin, and sometimes bradycardia and hypotension. Although miosis is characteristic of narcotic overdose, mydriasis may occur in terminal narcosis or severe hypoxia. In severe overdosage apnea, circulatory collapse, cardiac arrest and death may occur. The manifestations of chlorpheniramine overdosage may vary from central nervous system depression to stimulation.

Treatment

Primary attention should be given to the reestablishment of adequate respiratory exchange through provision of a patent airway and the institution of assisted or controlled ventilation. The narcotic antagonist naloxone hydrochloride is a specific antidote for respiratory depression which may result from overdosage or unusual sensitivity to narcotics including hydrocodone. Therefore, an appropriate dose of naloxone hydrochloride should be administered, preferably by the intravenous route, simultaneously with efforts at respiratory resuscitation. Since the duration of action of hydrocodone in this formulation may exceed that of the antagonist, the patient should be kept under continued surveillance and repeated doses of the antagonist should be administered as needed to maintain adequate respiration. For further information, see full prescribing information for naloxone hydrochloride. An antagonist should not be administered in the absence of clinically significant respiratory depression. Oxygen, intravenous fluids, vasopressors and other supportive measures should be employed as indicated. Gastric emptying may be useful in removing unabsorbed drug.

DOSAGE AND ADMINISTRATION

It is important that TUSSIONEX is measured with an accurate measuring device (see PRECAUTIONS, Information for Patients).

A dosing spoon is provided with the 4 oz (115 mL) packaged product. One side of the spoon is for a 2.5 mL dose. The other side of the spoon is for a 5 mL dose. Fill to level the side of the spoon for the dose that has been prescribed. Do not overfill. Rinse with water after each use.

For prescriptions where a dosing spoon is not provided, a pharmacist can provide an appropriate measuring device and can provide instructions for measuring the correct dose. A household teaspoon is not an accurate measuring device and could lead to overdosage.

Each 5 mL of TUSSIONEX Pennkinetic Extended-Release Suspension contains hydrocodone polistirex equivalent to 10 mg hydrocodone bitartrate, and chlorpheniramine polistirex equivalent to 8 mg chlorpheniramine maleate. Shake well before using. Rinse the measuring device with water after each use.

Adults and Children 12 Years and Older

5 mL every 12 hours; do not exceed 10 mL in 24 hours.

Children 6-11 Years of Age

2.5 mL every 12 hours; do not exceed 5 mL in 24 hours.

This medicine is contraindicated in children under 6 years of age (see CONTRAINDICATIONS).

HOW SUPPLIED

TUSSIONEX Pennkinetic (hydrocodone polistirex and chlorpheniramine polistirex) Extended-Release Suspension, equivalent to 10 mg hydrocodone bitartrate and 8 mg chlorpheniramine maleate per 5 mL, is a gold-colored suspension available as:

- NDC 53014-548-01 4 oz amber plastic bottle containing 115 mL of suspension. Each bottle is supplied with a plastic dosing spoon calibrated for measuring 2.5 mL and 5 mL doses.

For Medical Information

Contact: Medical Affairs Department
Phone: (866) 822-0068
Fax: (770) 970-8859

Storage

Store at 20 to 25°C (68 to 77°F); excursions permitted to 15 to 30°C (59 to 86°F) [see USP Controlled Room Temperature].

TUSSIONEX Pennkinetic Extended-Release Suspension
Manufactured for:
UCB, Inc.
Smyrna, GA 30080

TUSSIONEX and PENNKINETIC are registered trademarks of the UCB Group of companies.
© 2017, UCB, Inc., Smyrna, GA 30080. All rights reserved. Printed in the U.S.A.

Rev. 01/2017

MEDICATION GUIDE
TUSSIONEX® Pennkinetic ® (tuss-i-necks pen-ki-ne-tik)
(hydrocodone polistirex and chlorpheniramine polistirex)
Extended-Release Suspension CII

What is the most important information I should know about TUSSIONEX Pennkinetic Extended-Release Suspension?

- Taking TUSSIONEX Pennkinetic Extended-Release Suspension with benzodiazepines, or other central nervous system depressants, including alcohol can cause severe drowsiness, breathing problems (respiratory depression), coma, and death.
- TUSSIONEX Pennkinetic Extended-Release Suspension can cause you to be drowsy. Avoid driving a car or operating machinery during treatment with TUSSIONEX Pennkinetic Extended-Release Suspension.
- Women who breastfeed should talk to their healthcare provider before taking TUSSIONEX Pennkinetic Extended-Release Suspension.
- Call your healthcare provider or get emergency medical help right away if anyone taking TUSSIONEX Pennkinetic Extended-Release Suspension has any of the symptoms below:

- increased sleepiness
- confusion
- difficulty breathing

- shallow breathing
- limpness
- your baby has difficulty breastfeeding

- Keep TUSSIONEX Pennkinetic Extended-Release Suspension in a safe place away from children. Accidental use by a child is a medical emergency and can cause death. If a child accidentally takes TUSSIONEX Pennkinetic Extended-Release Suspension, get emergency medical help right away.
- TUSSIONEX Pennkinetic Extended-Release Suspension can cause serious side effects, including death.
- Take TUSSIONEX Pennkinetic Extended-Release Suspension exactly as prescribed by your healthcare provider. If you take the wrong dose of TUSSIONEX Pennkinetic Extended-Release Suspension, you could overdose and die.
- TUSSIONEX Pennkinetic Extended-Release Suspension is not for children under 6 years of age.

What is TUSSIONEX Pennkinetic Extended-Release Suspension?

- TUSSIONEX Pennkinetic Extended-Release Suspension is a prescription medicine used to treat cough and upper respiratory symptoms that you can have with allergies or a cold. TUSSIONEX Pennkinetic Extended-Release Suspension is for adults and children age 6 years and older. TUSSIONEX Pennkinetic Extended-Release Suspension contains 2 medicines, hydrocodone and chlorpheniramine. Hydrocodone is a narcotic cough suppressant. Chlorpheniramine is an antihistamine.
- TUSSIONEX Pennkinetic Extended-Release Suspension is a federal controlled substance (CII) because it contains hydrocodone that can be abused or lead to dependence. Keep TUSSIONEX Pennkinetic Extended-Release Suspension in a safe place to prevent misuse and abuse. Selling or giving away TUSSIONEX Pennkinetic Extended-Release Suspension may harm others, and is against the law. Tell your healthcare provider if you have abused or been dependent on alcohol, prescription medicines or street drugs.
- TUSSIONEX Pennkinetic Extended-Release Suspension is not for children under 6 years of age.

Who should not take TUSSIONEX Pennkinetic Extended-Release Suspension?

- Do not take TUSSIONEX Pennkinetic Extended-Release Suspension if you are allergic to any of the ingredients in TUSSIONEX Pennkinetic Extended-Release Suspension. See the end of this Medication Guide for a complete list of ingredients. You may have an increased risk of having an allergic reaction to TUSSIONEX Pennkinetic Extended-Release Suspension if you are allergic to certain other opioid medicines.
- Do not give TUSSIONEX Pennkinetic Extended-Release Suspension to a child under 6 years of age. It can cause breathing problems that can lead to death.

Before you take TUSSIONEX Pennkinetic Extended-Release Suspension, tell your healthcare provider about all of your medical conditions, including if you:

- have a drug dependence
- have lung or breathing problems
- have had a head injury
- have pain in your stomach-area (abdomen)
- have a history of severe or persistent cough
- have glaucoma
- have prostate problems
- have problems with your urinary tract (urethral stricture)

- plan to have surgery
- drink alcohol
- have kidney or liver problems
- have diabetes
- have thyroid problems, such as hypothyroidism
- Addison's disease

- are pregnant or plan to become pregnant. It is not known if TUSSIONEX Pennkinetic Extended-Release Suspension will harm your unborn baby. You and your healthcare provider should decide if you should take TUSSIONEX Pennkinetic Extended-Release Suspension while you are pregnant.
- are breastfeeding or plan to breastfeed. It is not known if TUSSIONEX Pennkinetic Extended-Release Suspension passes into your breast milk. You and your healthcare provider should decide if you will take TUSSIONEX Pennkinetic Extended-Release Suspension or breastfeed. You should not do both.

Tell your healthcare provider about all the medicines you take, including prescription and over-the-counter medicines, vitamins, and herbal supplements.

Taking TUSSIONEX Pennkinetic Extended-Release Suspension with certain other medicines can cause side effects or affect how well TUSSIONEX Pennkinetic Extended-Release Suspension or the other medicines work. Do not start or stop other medicines without talking to your healthcare provider.

Especially tell your healthcare provider if you:

- take pain medicines such as narcotics
- take cold or allergy medicines that contain antihistamines or cough suppressants
- take medicines for mental illness (anti-psychotics, anti-anxiety)
- drink alcohol
- take medicines for depression, including monoamine oxidase inhibitors (MAOIs) and tricyclics
- take medicines for stomach or intestine problems

Ask your healthcare provider if you are not sure if you take one of these medicines.

How should I take TUSSIONEX Pennkinetic Extended-Release Suspension?

- Take TUSSIONEX Pennkinetic Extended-Release Suspension exactly as your healthcare provider tells you to take it.
- Your healthcare provider will tell you how much TUSSIONEX Pennkinetic Extended-Release Suspension to take and when to take it. Do not change your dose without talking to your healthcare provider.
- Shake TUSSIONEX Pennkinetic Extended-Release Suspension well before each use.
- Do not mix TUSSIONEX Pennkinetic Extended-Release Suspension with other liquids or medicines. Mixing may change how TUSSIONEX Pennkinetic Extended-Release Suspension works.
- TUSSIONEX Pennkinetic Extended-Release Suspension can be taken with or without food.
- Only measure TUSSIONEX Pennkinetic Extended-Release Suspension with the dosing spoon that comes with your prescription. If you do not have a dosing spoon for your medicine, ask your pharmacist to give you a measuring device to help you measure the correct amount of TUSSIONEX Pennkinetic Extended-Release Suspension. Do not use a household teaspoon to measure your medicine. You may accidently take too much.
  - One side of the dosing spoon is marked for a 2.5 mL dose. The other side of the spoon is marked for a 5 mL dose. Find the side of the spoon that has the dose you are taking.
  - Fill that side of the spoon so the medicine is level with the rim of the spoon. Do not overfill the spoon.
  - Rinse the spoon with water after each use.
- If you take too much TUSSIONEX Pennkinetic Extended-Release Suspension, call your healthcare provider or go to the nearest hospital emergency room right away.

What should I avoid while taking TUSSIONEX Pennkinetic Extended-Release Suspension?

- TUSSIONEX Pennkinetic Extended-Release Suspension can cause you to be drowsy. Avoid driving a car or operating machinery during treatment with TUSSIONEX Pennkinetic Extended-Release Suspension.
- Avoid drinking alcohol during treatment with TUSSIONEX Pennkinetic Extended-Release Suspension. Drinking alcohol can increase your chances of having serious side effects.

What are the possible side effects of TUSSIONEX Pennkinetic Extended-Release Suspension?

TUSSIONEX Pennkinetic Extended-Release Suspension may cause serious side effects, including:

- See "What is the most important information I should know about TUSSIONEX Pennkinetic Extended-Release Suspension?"
- Breathing problems (respiratory depression) which can lead to death. Call your healthcare provider or get emergency treatment right away if you are sleeping more than usual, have shallow or slow breathing, or confusion.
- Increased intracranial pressure.
- Physical dependence or abuse. Take TUSSIONEX Pennkinetic Extended-Release Suspension exactly as your healthcare provider tells you to take it. Stopping TUSSIONEX Pennkinetic Extended-Release Suspension suddenly can cause withdrawal symptoms.
- Bowel problems including constipation or stomach pain.

The most common side effects of TUSSIONEX Pennkinetic Extended-Release Suspension include:

- sleepiness
- confusion
- nausea and vomiting
- difficulty urinating
- trouble breathing

These are not all the possible side effects of TUSSIONEX Pennkinetic Extended-Release Suspension.

Call your doctor for medical advice about side effects. You may report side effects to FDA at 1-800-FDA-1088.

How should I store TUSSIONEX Pennkinetic Extended-Release Suspension?

- Store TUSSIONEX Pennkinetic Extended-Release Suspension at room temperature between 68°F to 77°F (20°C to 25°C).
- Safely throw away medicine that is out of date or no longer needed.
- Keep TUSSIONEX Pennkinetic Extended-Release Suspension and all medicines out of the reach of children.

General information about the safe and effective use of TUSSIONEX Pennkinetic Extended-Release Suspension.

Medicines are sometimes prescribed for purposes other than those listed in a Medication Guide. Do not use TUSSIONEX Pennkinetic Extended-Release Suspension for a condition for which it was not prescribed. Do not give TUSSIONEX Pennkinetic Extended-Release Suspension to other people, even if they have the same symptoms that you have. It may harm them.

You can ask your pharmacist or healthcare provider for information about TUSSIONEX Pennkinetic Extended-Release Suspension that is written for health professionals.

What are the ingredients in TUSSIONEX Pennkinetic Extended-Release Suspension?

Active Ingredient: hydrocodone polistirex and chlorpheniramine polistirex

Inactive Ingredients: Ascorbic acid, D&C Yellow No. 10, ethylcellulose, FD&C Yellow No. 6, flavor, high fructose corn syrup, methylparaben, polyethylene glycol 3350, polysorbate 80, pregelatinized starch, propylene glycol, propylparaben, purified water, sucrose, vegetable oil, xanthan gum.

Manufactured for: UCB, Inc. Smyrna, GA 30080
For more information about TUSSIONEX Pennkinetic Extended-Release Suspension call 1-844-599-2273.

This Medication Guide has been approved by the U.S. Food and Drug Administration.

Issued: January 2017

PRINCIPAL DISPLAY PANEL - 115 mL Bottle Label

NDC 53014-548-01
Rx ONLY

CII

Tussionex®
Pennkinetic®
(hydrocodone polistirex and
chlorpheniramine polistirex)
Extended-Release Suspension

equivalent to 10 mg hydrocodone
bitartrate/8 mg chlorpheniramine
maleate per 5 mL

Nonalcoholic
12-hour Dosing

Contraindicated in
children under
6 years of age

Dispense enclosed
Medication Guide to
each patient.

Dispense entire carton
as one unit

4 oz. (115 mL)